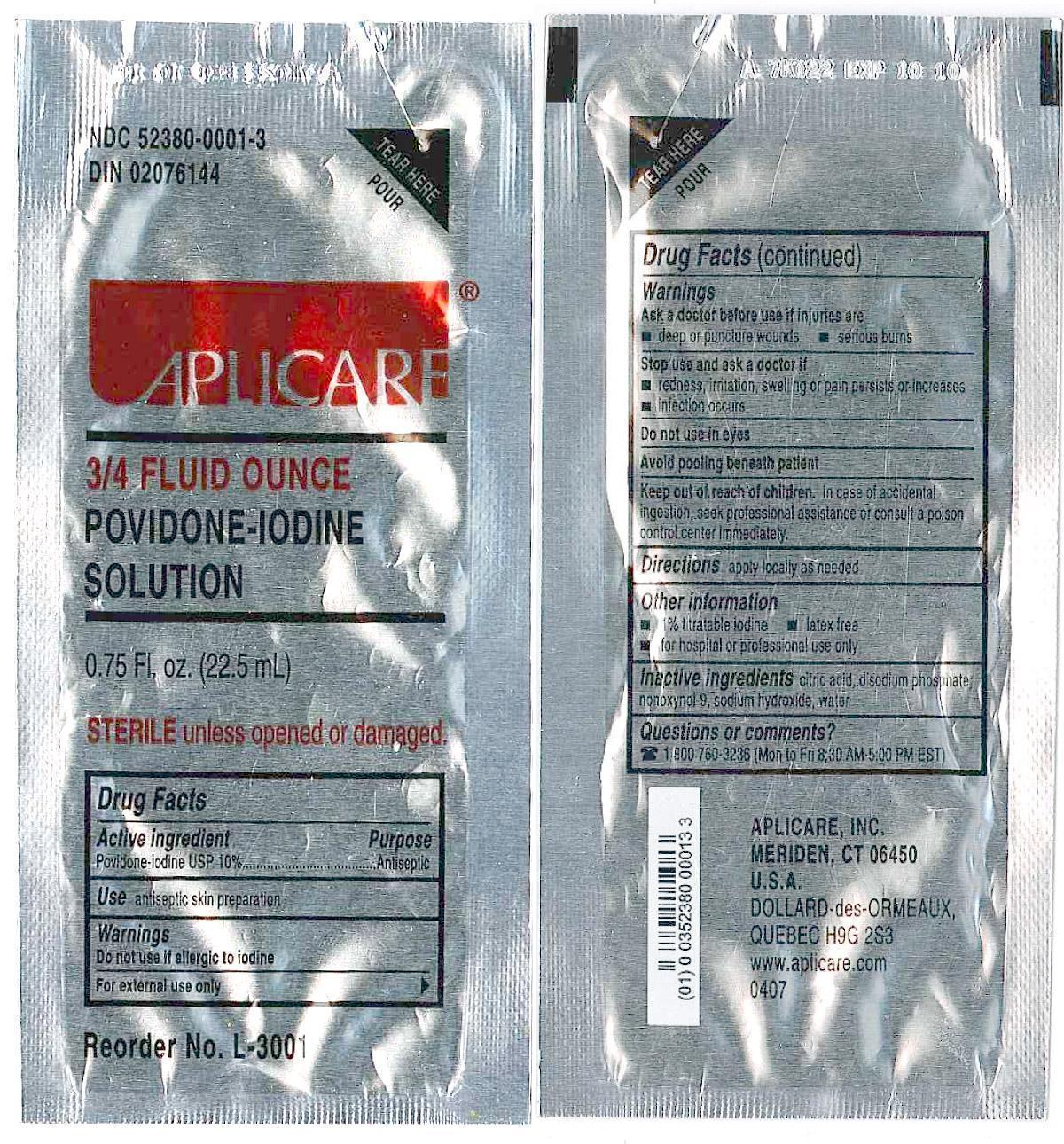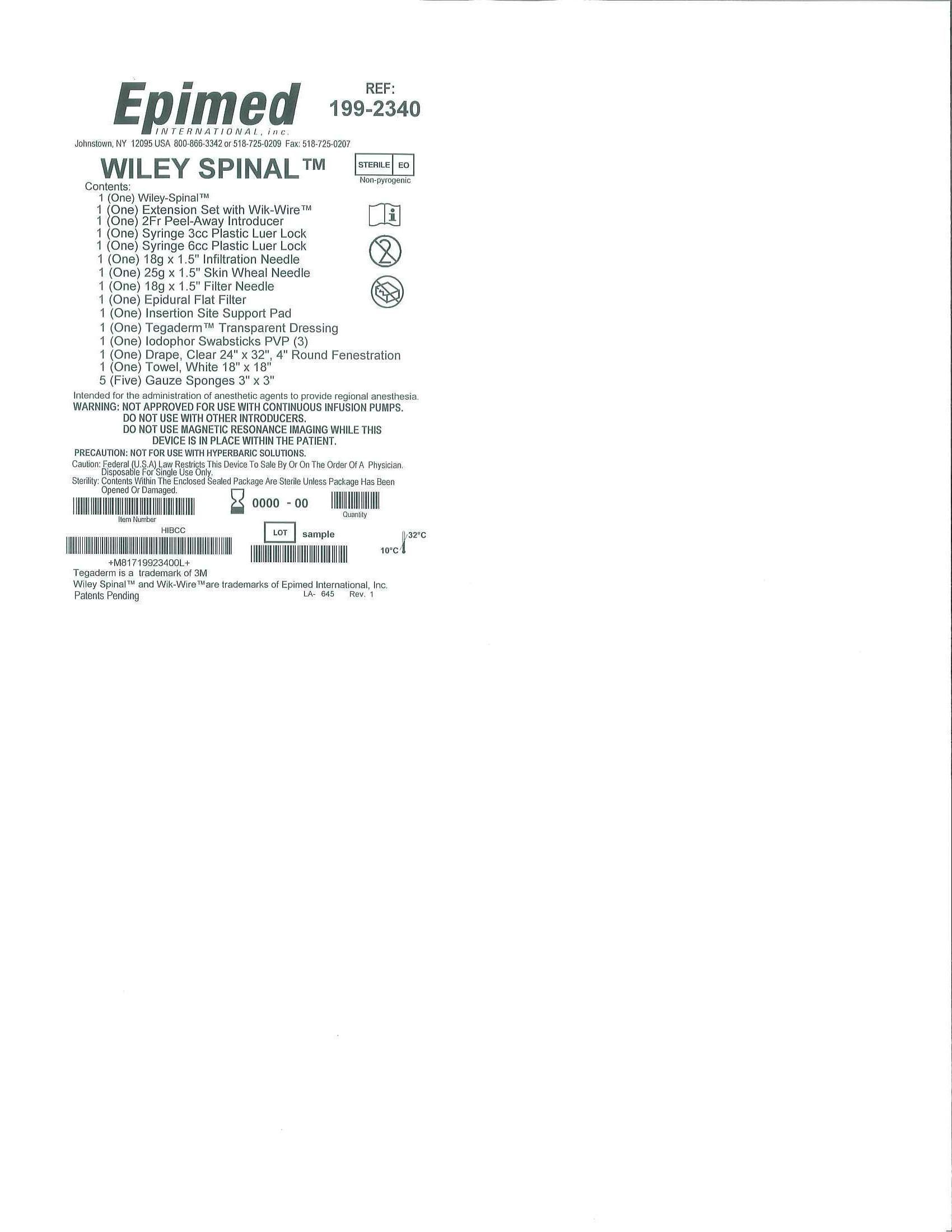 DRUG LABEL: Wiley Spinal
NDC: 60816-2340 | Form: KIT | Route: TOPICAL
Manufacturer: Epimed International
Category: other | Type: MEDICAL DEVICE
Date: 20130930

ACTIVE INGREDIENTS: Povidone-iodine 10 mg/1 mL
INACTIVE INGREDIENTS: CITRIC ACID MONOHYDRATE; SODIUM PHOSPHATE, DIBASIC; SODIUM HYDROXIDE; NONOXYNOL-9; WATER

DESCRIPTION

APLICARE POVIDONE-IODINE SOLUTION (povidone-iodine solution) solution
[Aplicare, Inc.]

3/4 Ounce Povidone Iodine Packet

WARNINGS

Povidone-iodine 10%

Antiseptic

Warnings

Do not use

- if allergic to iodine
- in the eyes

For external use only

Ask a doctor before use if injuries are

- deep or puncture wounds
- serious burns

Stop use and ask a doctor if

- redness, irritation, swelling or pain persists or increases
- infection occurs

Avoid pooling beneath patient

Keep out of reach of children.In case of accidental ingestion, seek professionalassistance or consult a poison control center immediately.

Package Label Display Panel